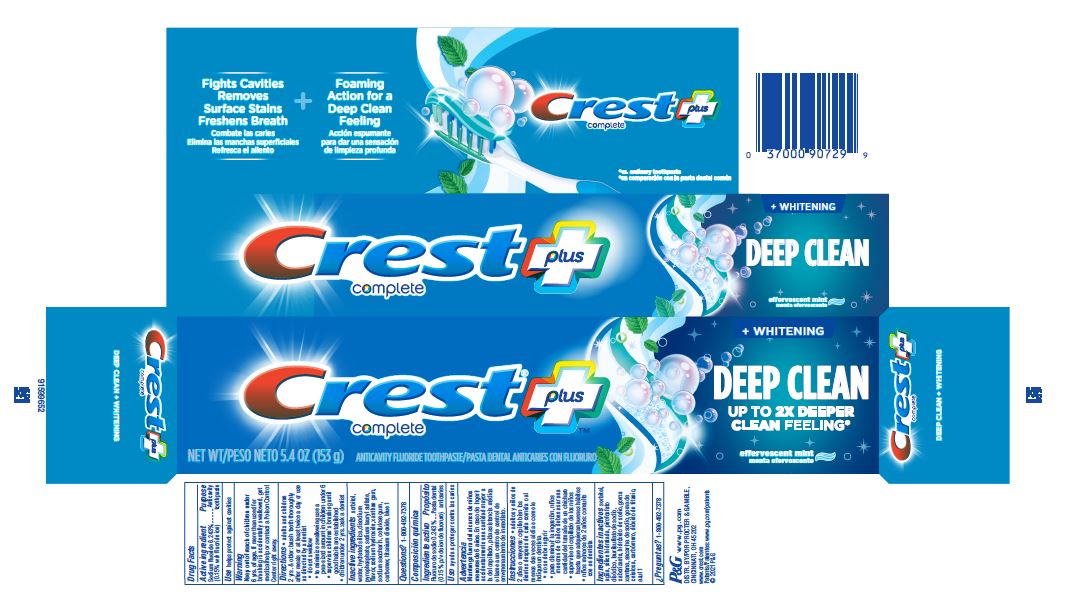 DRUG LABEL: Crest Complete plus
NDC: 69423-911 | Form: PASTE, DENTIFRICE
Manufacturer: The Procter & Gamble Manufacturing Company
Category: otc | Type: HUMAN OTC DRUG LABEL
Date: 20250108

ACTIVE INGREDIENTS: SODIUM FLUORIDE 1.5 mg/1 g
INACTIVE INGREDIENTS: SODIUM HYDROXIDE; SACCHARIN SODIUM; SODIUM ACID PYROPHOSPHATE; SODIUM LAURYL SULFATE; XANTHAN GUM; CARBOXYPOLYMETHYLENE; SORBITOL; FD&C BLUE NO. 1; WATER; HYDRATED SILICA; TITANIUM DIOXIDE; CARBOXYMETHYLCELLULOSE SODIUM

Crest Complete plus Whitening Deep Clean

Drug Facts

Active ingredient

Sodium fluoride 0.243%

(0.15% w/v fluoride ion)

Purpose

Anticavity toothpaste

Use

helps protect against cavities

Warnings

Keep out of reach of children under 6 yrs. of age. If more than used for brushing is accidentally swallowed, get medical help or contact a Poison Control Center right away.

Directions

- adults and children 2 yrs. & older: brush teeth thoroughly after meals or at least twice a day or use as directed by a dentist
  - do not swallow
  - to minimize swallowing use a pea-sized amount in children under 6
  - supervise children's brushing until good habits are established
- children under 2 yrs.: ask a dentist

Inactive ingredients

sorbitol, water, hydrated silica, disodium pyrophosphate, sodium lauryl sulfate, flavor, sodium hydroxide, xanthan gum, sodium saccharin, cellulose gum, carbomer, titanium dioxide, blue 1

Questions?

1-800-492-7378

DISTR. BY PROCTER & GAMBLE,
CINCINNATI, OH 45202

PRINCIPAL DISPLAY PANEL - 153 g Carton

Crest ®

complete

plus™

NET WT 5.4 OZ (153 g)

ANTICAVITY FLUORIDE TOOTHPASTE
+ WHITENING

DEEP CLEAN

UP TO 2X DEEPER CLEAN FEELING*

effervescent mint